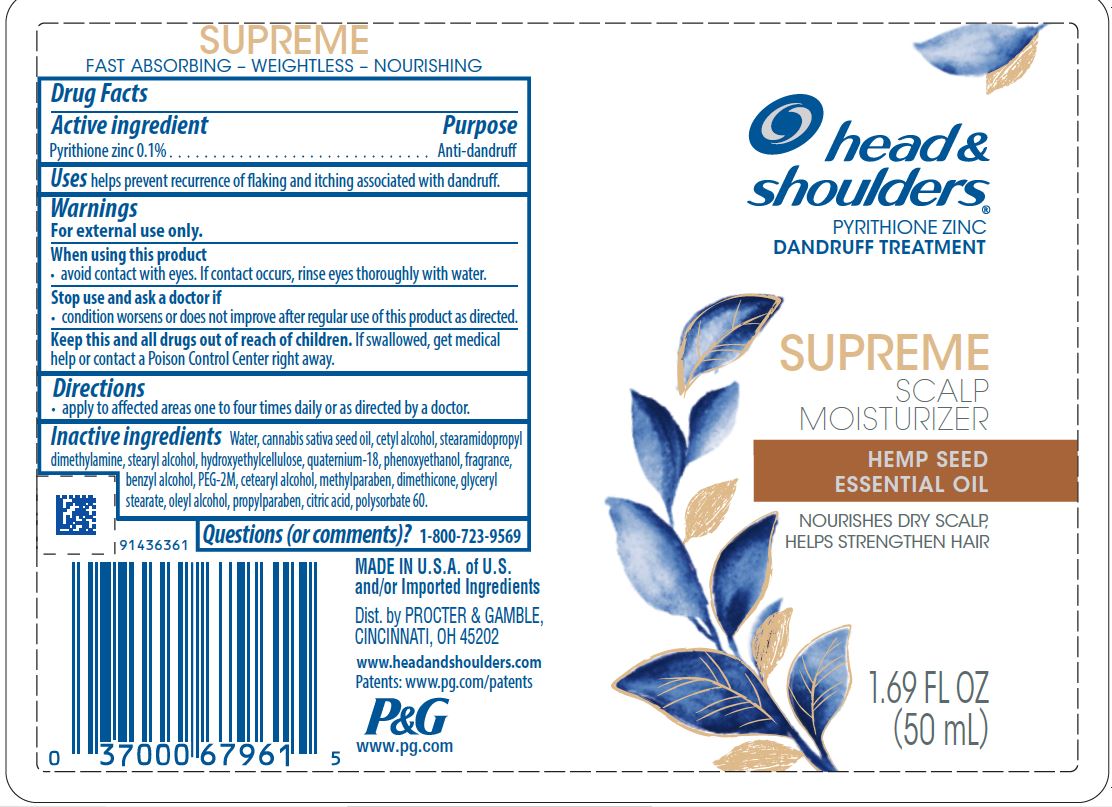 DRUG LABEL: Head and Shoulders Supreme Scalp Moisturizer with Hemp Seed
NDC: 69423-569 | Form: LOTION
Manufacturer: The Procter & Gamble Manufacturing Company
Category: otc | Type: HUMAN OTC DRUG LABEL
Date: 20210727

ACTIVE INGREDIENTS: PYRITHIONE ZINC 0.1 g/100 mL
INACTIVE INGREDIENTS: STEARAMIDOPROPYL DIMETHYLAMINE; HYDROXYETHYL CELLULOSE, UNSPECIFIED; POLYSORBATE 60; CITRIC ACID MONOHYDRATE; METHYLPARABEN; PHENOXYETHANOL; POLYETHYLENE OXIDE 100000; OLEYL ALCOHOL; PROPYLPARABEN; QUATERNIUM-18; CETOSTEARYL ALCOHOL; STEARYL ALCOHOL; CETYL ALCOHOL; WATER; CANNABIS SATIVA SEED OIL; BENZYL ALCOHOL; GLYCERYL MONOSTEARATE; DIMETHICONE

Head and Shoulders® Supreme Scalp Moisturizer Hemp Seed Essential Oil

Drug Facts

Active ingredient

Pyrithione zinc 0.1%

Purpose

Anti-dandruff

Uses

helps prevent recurrence of flaking and itching associated with dandruff.

Warnings

For external use only.

When using this product

- avoid contact with eyes. If contact occurs, rinse eyes thoroughly with water.

Stop use and ask a doctor if

- condition worsens or does not improve after regular use of this product as directed.

KEEP OUT OF REACH OF CHILDREN

Keep this and all drugs out of reach of children. If swallowed, get medical help or contact a Poison Control Center right away.

Directions

• apply to affected areas one to four times daily or as directed by a doctor.

Inactive ingredients

Water, cannabis sativa seed oil, cetyl alcohol, stearamidopropyl dimethylamine, stearyl alcohol, hydroxyethylcellulose, quaternium-18, phenoxyethanol, fragrance, benzyl alcohol, PEG-2M, cetearyl alcohol, methylparaben, dimethicone, glyceryl stearate, oleyl alcohol, propylparaben, citric acid, polysorbate 60.

Questions (or comments)?

1-800-723-9569

Dist. by PROCTER & GAMBLE,
CINCINNATI, OH 45202

PRINCIPAL DISPLAY PANEL - 50 mL bottle label

Head & Shoulders

PYRITHIONE ZINC DANDRUFF TREATMENT

SUPREME SCALP MOISTURIZER

HEMP OIL ESSENTIAL OIL

NOURISHES DRY SCALP,

HELPS STRENGTHEN HAIR

1.69 FL OZ (50 mL)